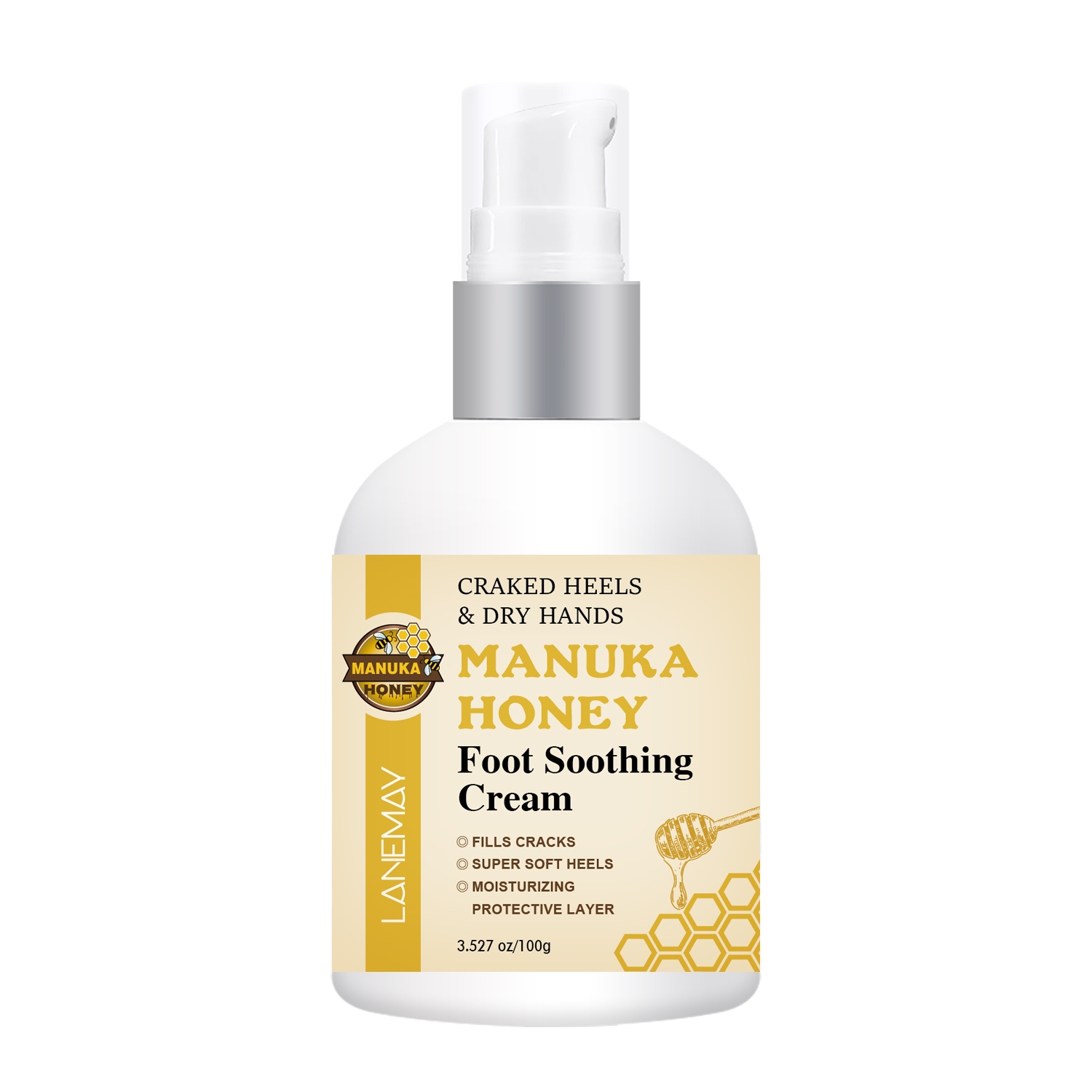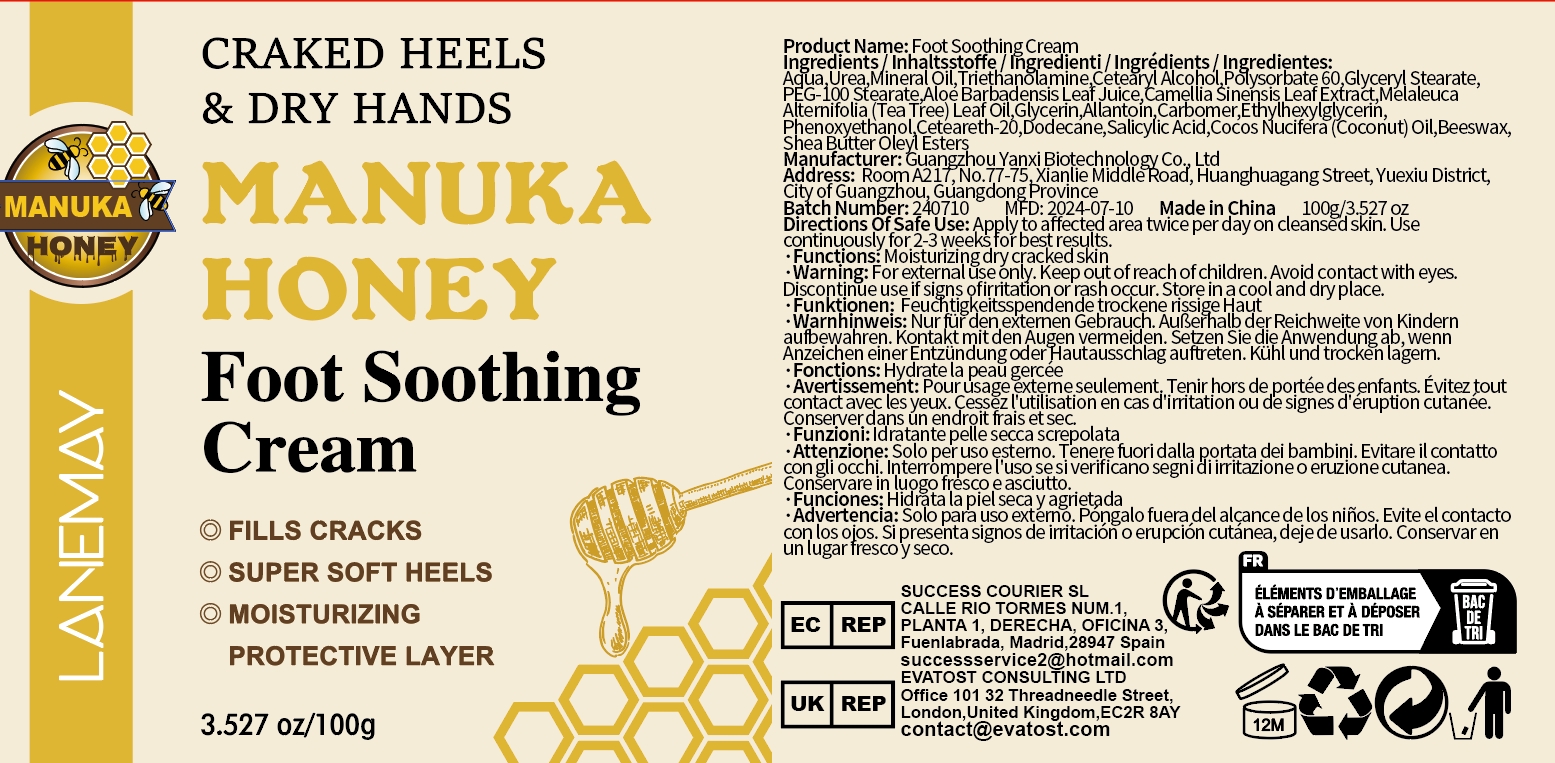 DRUG LABEL: Foot Soothing Cream
NDC: 84025-072 | Form: CREAM
Manufacturer: Guangzhou Yanxi Biotechnology Co.. Ltd
Category: otc | Type: HUMAN OTC DRUG LABEL
Date: 20240720

ACTIVE INGREDIENTS: MINERAL OIL 5 mg/100 g; POLYSORBATE 60 3 mg/100 g
INACTIVE INGREDIENTS: WATER

DOSAGE AND ADMINISTRATION

Used to protect the feet

WARNINGS

keep out of children

INACTIVE INGREDIENT

Aqua

INDICATIONS AND USAGE

Repair foot skin damage

keep out of children

PURPOSE

Protects feet, repairs and moisturizes foot skin